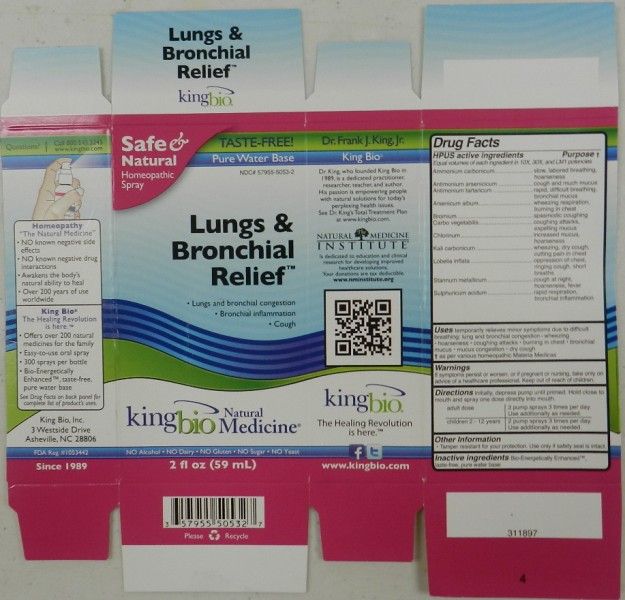 DRUG LABEL: Lungs and Bronchial Relief
NDC: 57955-5053 | Form: LIQUID
Manufacturer: King Bio Inc
Category: homeopathic | Type: HUMAN OTC DRUG LABEL
Date: 20111020

ACTIVE INGREDIENTS: AMMONIUM CARBONATE 10 [hp_X]/59 mL; ANTIMONY ARSENATE 10 [hp_X]/59 mL; ANTIMONY POTASSIUM TARTRATE 10 [hp_X]/59 mL; ARSENIC TRIOXIDE 10 [hp_X]/59 mL; BROMINE 10 [hp_X]/59 mL; ACTIVATED CHARCOAL 10 [hp_X]/59 mL; CHLORINE 10 [hp_X]/59 mL; POTASSIUM CARBONATE 10 [hp_X]/59 mL; LOBELIA INFLATA 10 [hp_X]/59 mL; TIN 10 [hp_X]/59 mL; SULFURIC ACID 10 [hp_X]/59 mL
INACTIVE INGREDIENTS: WATER

Lungs and Bronchial Relief

OTC Active Ingredient

HPUS active ingredients

Equal volumes of each ingredient in 10X, 30X, and LM1 potencies

Ammonium carbonicum

Antimonium arsenicicum

Antimonium tartaricum

Arsenicum album

Bromium

Carbo vegetabilis

Chlorinum

Kali carbonicum

Lobelia inflata

Stannum metallicum

Sulphuricum acidum

Reference image lung.jpg

Inactive Ingredient

Bio-Energetically Enhanced taste-free, pure water base

Reference image lung.jpg

Dosage and Administration

Directions: Initially, depress pump until primed. Hold close to mouth and spray one dose directly into mouth.

Adult Dose 3 pump sprays 3 times per day. Use additionally as needed.

Children 2-12 years 2 pump sprays 3 times per day. Use additionally as needed.

Reference image lung.jpg

OTC Purpose

HPUS active ingredients Purpose

Ammonium carbonicum........slow, labored breathing, hoarseness

Antimonium arsenicicum.......cough and much mucus

Antimonium tartaricum...........rapid, difficult breathing, bronchial mucus

Arsenicum album.................wheezing respiration, burning in chest

Bromium.............................spasmodic coughing

Carbo vegetabilis.................coughing attacks, expelling mucus

Chlorinum............................increased mucus, hoarseness

Kali carbonicum..................wheezing, dry cough, cutting pain in chest

Lobelia inflata......................oppression of chest, ringing cough, short breaths

Stannum metallicum............cough at night, hoarseness, fever

Sulphuricum acidum............rapid respiration, bronchial inflammation

Reference image lung.jpg

Warnings

If symptoms persist or worsen, or if pregnant or nursing, take only on advice of a healthcare professional. Keep out of reach of children.

Other Information

Tamper resistant for your protection. Use only if safety seal is intact.

Reference image lung.jpg

OTC Keep Out of Reach of Children

Keep out of reach of children.

Reference image lung.jpg

Indication and usage

Uses: temporarily relieves minor symptoms due to difficult breathing:

- lung and bronchial congestion
- wheezing
- hoarseness
- coughing attacks
- burning in chest
- bronchial mucus
- mucus congestion
- dry cough

as per various homeopathic Materia Medicas
Reference image lung.jpg

Package Label Principal Display

King Bio Inc.

3 Westside Drive

Asheville, NC 28806

WWW.kingbio.com

Reference image lung.jpg